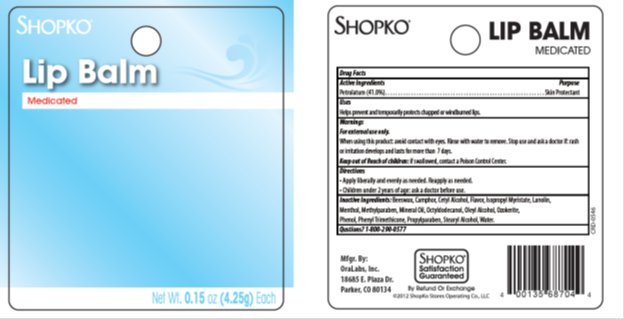 DRUG LABEL: Shopko Medicated Lip Balm
NDC: 37012-737 | Form: STICK
Manufacturer: Shopko
Category: otc | Type: HUMAN OTC DRUG LABEL
Date: 20130724

ACTIVE INGREDIENTS: PETROLATUM 41 mg/1 g
INACTIVE INGREDIENTS: CERESIN 16 mg/1 g; APIS CERANA WORKER SECRETION 6 mg/1 g; OLEYL ALCOHOL 6 mg/1 g; ISOPROPYL MYRISTATE 5 mg/1 g; OCTYLDODECANOL 9 mg/1 g; LANOLIN 4 mg/1 g; STEARYL ALCOHOL 3 mg/1 g; CETYL ALCOHOL 3 mg/1 g; LIGHT MINERAL OIL 3 mg/1 g; MENTHOL .60 mg/1 g

Drug Facts

Active ingredient

Petrolatum

Purpose

Skin Protectant

Keep Out of Reach of Children

If swallowed, contact a Poison Control Center.

Uses

Helps prevent and temporarily protects chapped or windburned lips.

Warnings

For external use only.

When using this product: avoid contact with eyes. Rinse with water to remove. Stop use and ask a doctor if :rash or irritation develops and lasts for more than 7 days. .

Directions

Apply liberally and evenly as needed. Children under 2 years of age: ask doctor before use.

Inactive Ingredients

Beeswax, Camphor, Cetyl Alcohol, Flavor, Ispropyl Myristate, Lanolin, Menthol, Methylparaben, Mineral Oil, Octyldodecanol, Oleyl Alcohol, Ozokerite, Phenol, Phenyl Trimethicone, Propylparaben, Stearyl Alcohol, Water